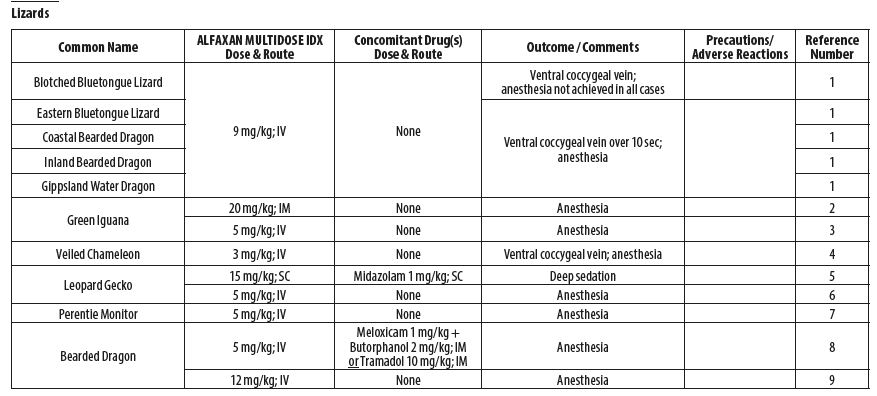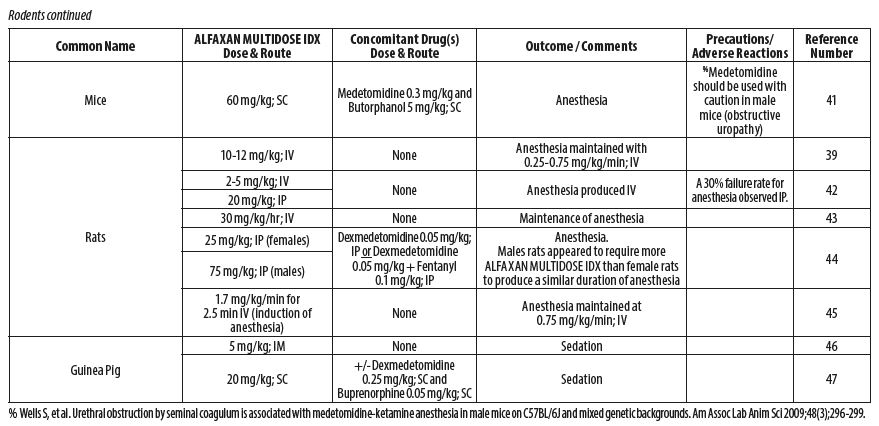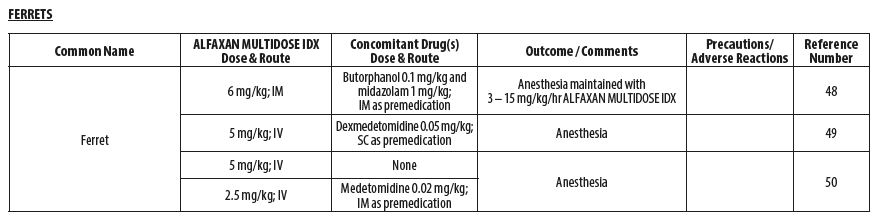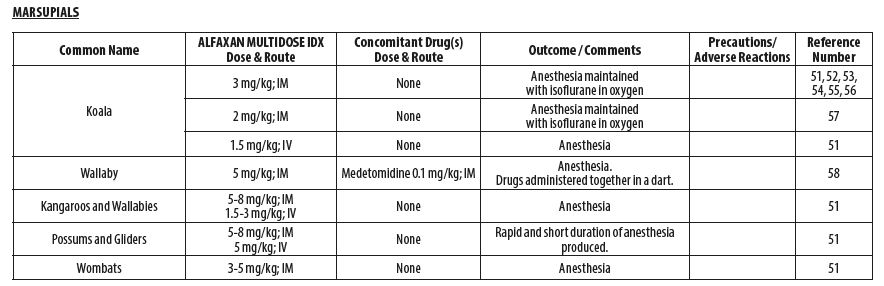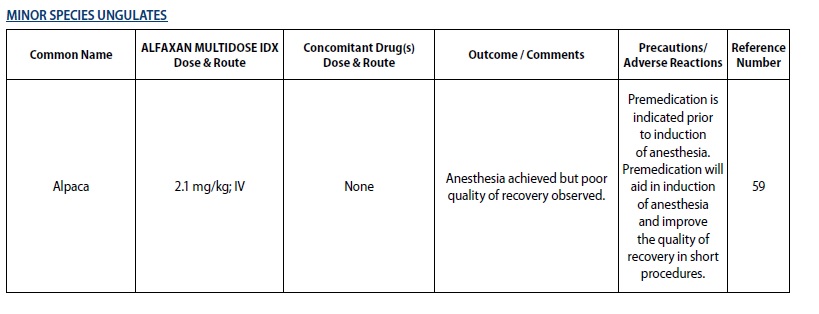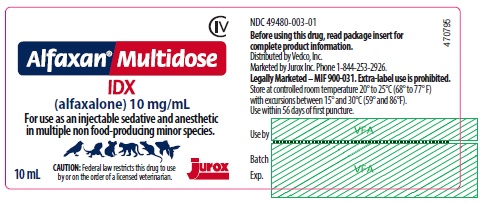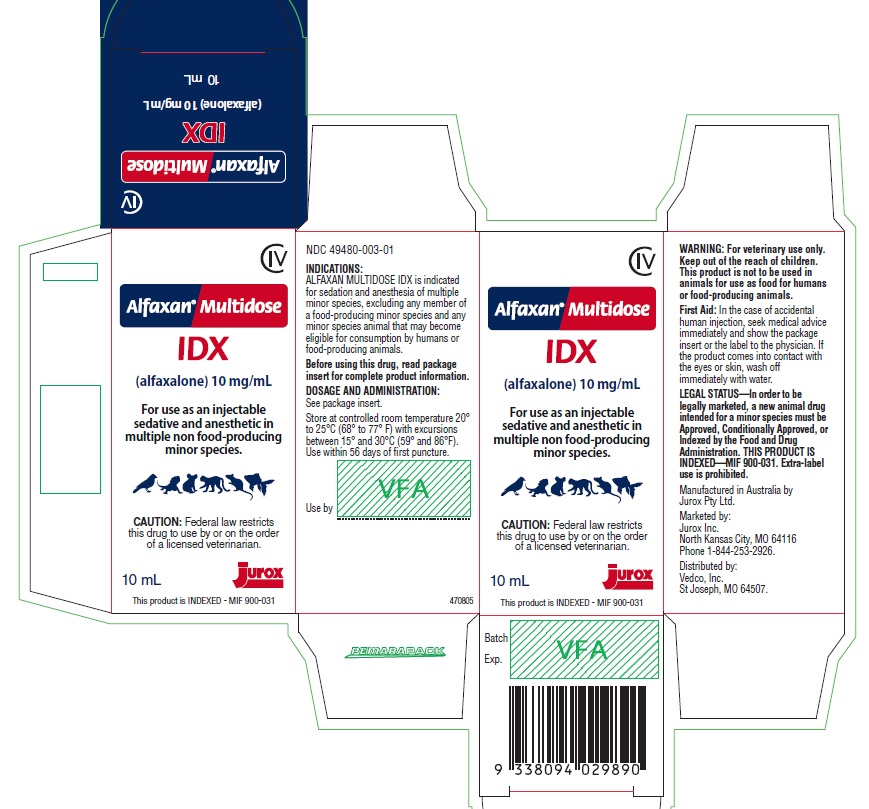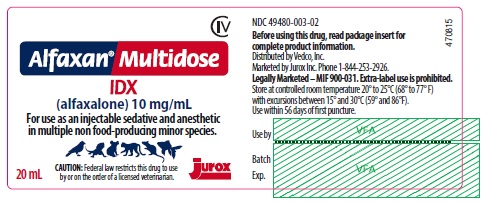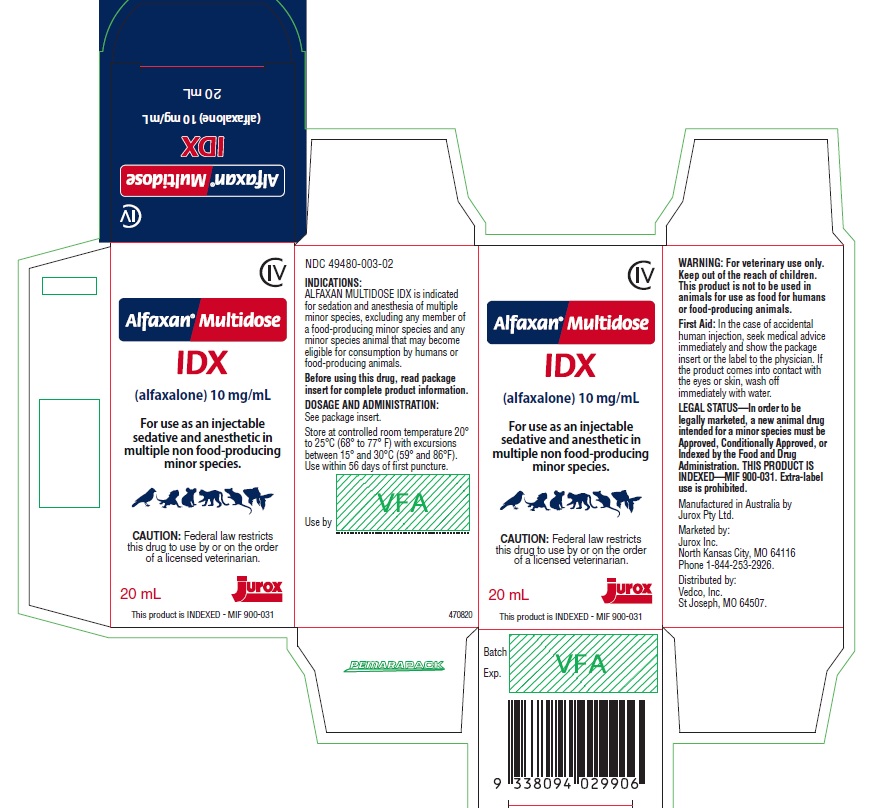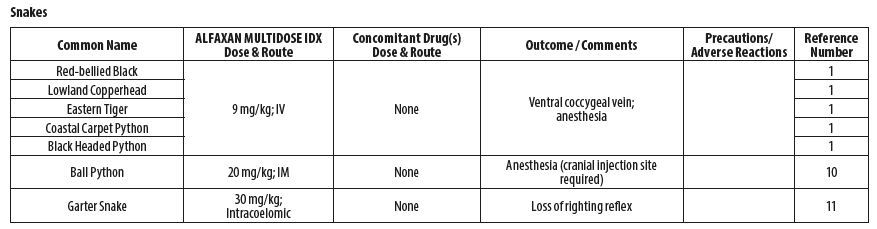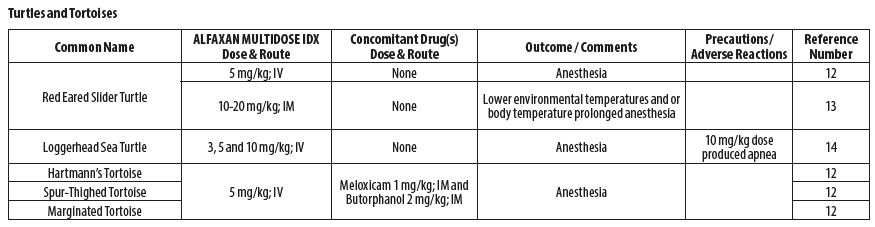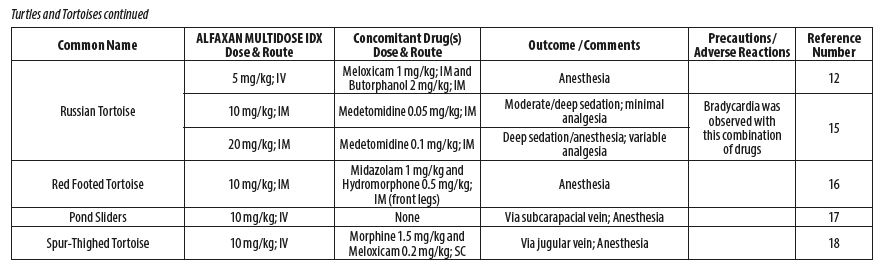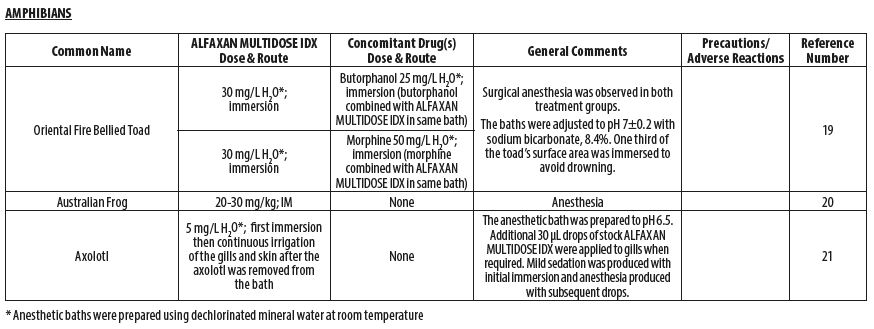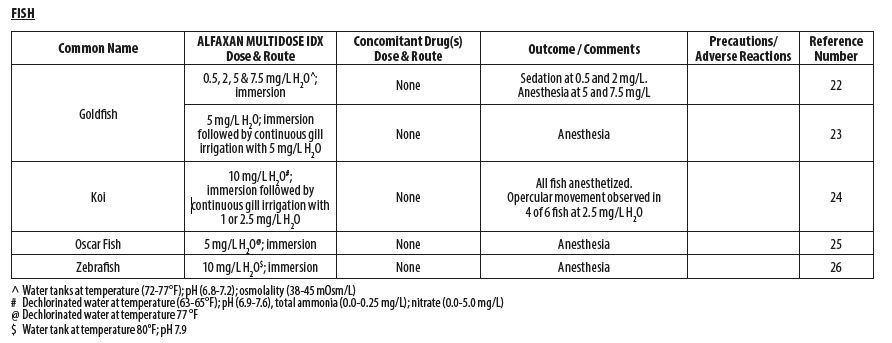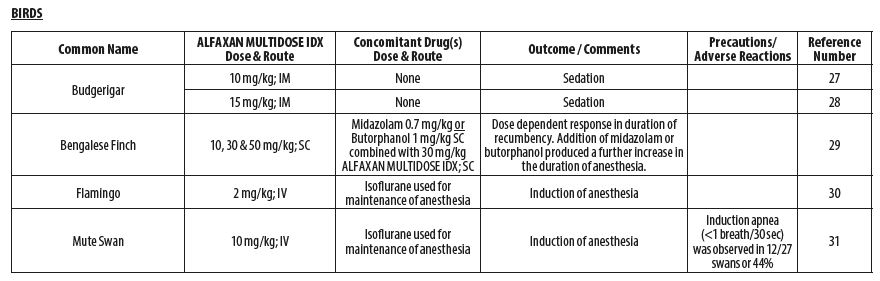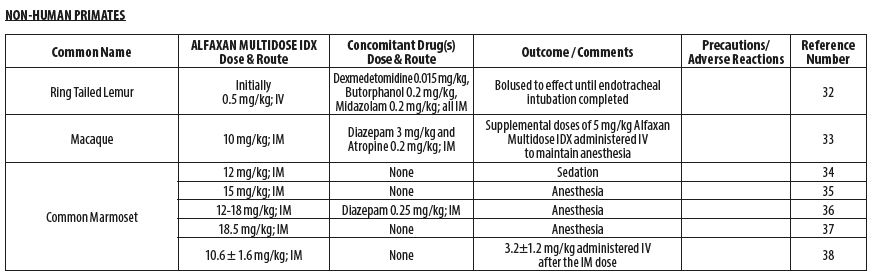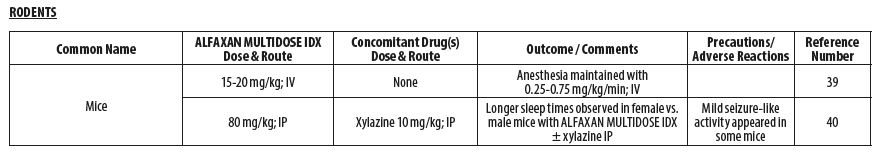 DRUG LABEL: ALFAXAN
NDC: 49480-003 | Form: SOLUTION
Manufacturer: Jurox Pty. Limited
Category: animal | Type: PRESCRIPTION ANIMAL DRUG LABEL
Date: 20240205
DEA Schedule: CIV

ACTIVE INGREDIENTS: ALFAXALONE 10 mg/1 mL
INACTIVE INGREDIENTS: HYDROXYPROPYLBETADEX (0.58-0.68 MS) 80 mg/1 mL; SODIUM CHLORIDE; SODIUM PHOSPHATE, DIBASIC, ANHYDROUS; ALCOHOL 150 mg/1 mL; BENZETHONIUM CHLORIDE 0.2 mg/1 mL; CHLOROCRESOL 1 mg/1 mL; POTASSIUM PHOSPHATE, MONOBASIC; HYDROCHLORIC ACID

ALFAXAN MULTIDOSE IDX

GENERAL PRECAUTIONS

FOR ANIMAL USE ONLY

Alfaxan® Multidose IDX CIV

(alfaxalone) 10 mg/mL Injectable Solution

For use as an injectable sedative and anesthetic in multiple non food-producing minor species.

CAUTION: Federal law restricts this drug to use by or on the order of a licensed veterinarian.

LEGAL STATUS: In order to be legally marketed, a new animal drug intended for a minor species must be Approved, Conditionally Approved, or Indexed by the Food and Drug Administration. THIS PRODUCT IS INDEXED—MIF 900-031. Extra-label use is prohibited.

This product is not to be used in animals for use as food for humans or food-producing animals.

DESCRIPTION

ALFAXAN MULTIDOSE IDX contains alfaxalone, a neuroactive steroid molecule with properties of a general anesthetic. Alfaxalone is chemically described as 3‑ α‑ hydroxy‑ 5‑ α‑ pregnane‑ 11, 20‑dione, and has a molecular weight of 332.5. The primary mechanism for the anesthetic action of alfaxalone is modulation of neuronal cell membrane chloride ion transport, induced by binding of alfaxalone to GABAA (gamma‑aminobutyric acid) cell surface receptors. This product contains the following preservatives: chlorocresol (0.1% w/v), benzethonium chloride (0.02% w/v) and ethanol (15% w/v).

INDICATIONS

ALFAXAN MULTIDOSE IDX is indicated as a sedative and anesthetic in multiple minor species*. More specifically, ALFAXAN MULTIDOSE IDX is indicated for the following:

- For sedation and anesthesia in captive reptiles, excluding any food‑producing species**
- For sedation and anesthesia in captive amphibians, excluding any food‑producing species**
- For sedation and anesthesia in ornamental fish, including species used in research such as the zebrafish
- For sedation and anesthesia in captive species and pet birds in the orders Psittaciformes, Passeriformes, and Columbiformes, excluding any food‑producing species**
- For sedation and anesthesia in non‑human primates
- For sedation and anesthesia in captive rodents
- For sedation and anesthesia in captive mustelids
- For sedation and anesthesia in captive marsupials
- For induction of anesthesia and immobilization in captive minor species ungulates, excluding any food‑producing species**

Use only when there is reasonable certainty that the treated animal will not be consumed by humans or food‑producing animals.

* The term “minor species” means animals other than humans that are not major species. “Major species” means cattle, horses, swine, chickens, turkeys, dogs and cats.

** As used on this label, a “food‑producing minor species” is considered to be a minor species of which some members are bred, cultured, farmed, ranched, hunted, caught, trapped or otherwise harvested for the purpose of having the animals or edible products of the animals commercially distributed for consumption by humans or food‑producing animals in the United States.

DOSAGE AND ADMINISTRATION

When administering ALFAXAN MULTIDOSE IDX by intravenous injection administer slowly to effect, titrating administration against the response of the patient. Rapid administration of ALFAXAN MULTIDOSE IDX may be associated with an increased incidence of cardiorespiratory depression or apnea. The use of preanesthetics may reduce the ALFAXAN MULTIDOSE IDX induction dose. The choice and the amount of phenothiazine, alpha₂‑ adrenoreceptor agonist, benzodiazepine or opioid will influence the response of the patient to an induction dose of ALFAXAN MULTIDOSE IDX.

When using ALFAXAN MULTIDOSE IDX, patients should be continuously monitored, and facilities for the maintenance of a patent airway, artificial ventilation, and oxygen supplementation must be immediately available.

ALFAXAN MULTIDOSE IDX contains preservatives. Use within 56 days of first puncture. Any unused ALFAXAN MULTIDOSE IDX remaining after 56 days should be discarded.

The following tables outline the dosage and administration of ALFAXAN MULTIDOSE IDX for the indicated species by major group. The doses are representative of doses published in the literature. Veterinarians are advised to consult the published literature before use of the product (see List of References at end of product insert).

DRUG INTERACTIONS

No specific preanesthetic is either indicated or contraindicated with ALFAXAN MULTIDOSE IDX. The necessity for and choice of preanesthetic is left to the discretion of the veterinarian. Preanesthetic doses may be lower than the label directions for their use as a single medication. ALFAXAN MULTIDOSE IDX is compatible with benzodiazepines, opioids, alpha2‑agonists, and phenothiazines as commonly used in surgical practice.

CONTRAINDICATIONS

ALFAXAN MULTIDOSE IDX is contraindicated in animals with a known sensitivity to ALFAXAN MULTIDOSE IDX or its components, or when general anesthesia and/or sedation are contraindicated. Do not use in any minor species animal that may become eligible for consumption by humans or food‑producing animals.

WARNINGS

Animal Safety: Rapid bolus administration or anesthetic overdose may cause cardiorespiratory depression, including hypotension, apnea, hypoxia, or death. Arrhythmias may occur secondary to apnea and hypoxia. In cases of anesthetic overdose, stop ALFAXAN MULTIDOSE IDX administration and administer treatment as indicated by the patient’s clinical signs. Cardiovascular depression should be treated with plasma expanders, pressor agents, anti‑arrhythmic agents or other techniques as appropriate for the treatments of the clinical signs

Human safety: Not for human use. Keep out of the reach of children.

ALFAXAN MULTIDOSE IDX should be managed to prevent the risk of diversion, through such measures as restriction of access and the use of drug accountability procedures appropriate to the clinical setting.

Exercise caution to avoid accidental self‑injection. Overdose is likely to cause cardiorespiratory depression (such as hypotension, bradycardia and/ or apnea). Remove the individual from the source of exposure and seek medical attention. Respiratory depression should be treated by artificial ventilation and oxygen. Avoid contact of this product with skin, eyes, and clothes. In case of contact, eyes and skin should be liberally flushed with water for 15 minutes. Consult a physician if irritation persists. In the case of accidental human ingestion, seek medical advice immediately and show the package insert or the label to the physician.

The Safety Data Sheet (SDS) contains more detailed occupational safety information. To report adverse reactions in users or to obtain a copy of the SDS for this product call 1‑844‑253‑2926.

Note to physician: This product contains an injectable anesthetic.

DRUG ABUSE AND DEPENDENCE

Controlled substance: ALFAXAN MULTIDOSE IDX contains alfaxalone a neurosteroid anesthetic and a class IV controlled substance.
Abuse: Alfaxalone is a central nervous system depressant that acts on GABA receptor associated chloride channels, similar to the mechanism of action of Schedule IV sedatives such as benzodiazepines (diazepam and midazolam), barbiturates (phenobarbital and methohexital) and fospropofol. In a drug discrimination behavioral test in rats, the effects of alfaxalone were recognized as similar to those of midazolam. These biochemical and behavioral data suggest that alfaxalone has an abuse potential similar to other Schedule IV sedatives.
Physical dependence: There are no data that assess the ability of alfaxalone to induce physical dependence. However, alfaxalone has a mechanism of action similar to the benzodiazepines and can block the behavioral responses associated with precipitated benzodiazepine withdrawal. Therefore, it is likely that alfaxalone can also produce physical dependence and withdrawal signs similar to that produced by the benzodiazepines.
Psychological dependence: The ability of alfaxalone to produce psychological dependence is unknown because there are no data on the rewarding properties of the drug from animal self-administration studies or from human abuse potential studies.

PRECAUTIONS

Analgesia during anesthesia: ALFAXAN MULTIDOSE IDX is not an analgesic and appropriate analgesia should be provided to the patient for painful procedures.

Rapid arousal: Careful monitoring of the patient is necessary due to possibility of rapid arousal.

Apnea: Apnea may occur following IV administration of an induction dose, maintenance dose or a dose administered during transition to inhalant maintenance anesthesia of ALFAXAN MULTIDOSE IDX, especially with higher doses and rapid administration. Endotracheal intubation, oxygen supplementation and intermittent positive pressure ventilation (IPPV) should be administered to treat apnea and associated hypoxemia in the appropriate species.

Blood Pressure: ALFAXAN MULTIDOSE IDX can exacerbate the myocardial depressive and vasodilatory effects of inhalant anesthetics resulting in hypotension. Preanesthetics can potentiate the effect of ALFAXAN MULTIDOSE IDX resulting in more pronounced changes in blood pressure. Transient hypertension has also been observed with ALFAXAN MULTIDOSE IDX administration, possibly due to elevated sympathetic activity in the patient. It is prudent to monitor blood pressure whenever possible.

Body temperature: Steps should be taken to maintain the normal physiological temperature of the patient during anesthesia. Supplemental heat, appropriate for the species, should be provided to maintain acceptable core body temperature until full recovery.

Breeding animals: Alfaxalone crosses the placenta, and as with other general anesthetic agents, the administration of ALFAXAN MULTIDOSE IDX may be associated with neonatal depression.

Compromised or debilitated animals: Caution should be used in animals with cardiac, respiratory, renal or hepatic impairment, or in hypovolemic or debilitated animals and geriatric animals.

ADVERSE REACTIONS

Specific adverse reactions described in the referenced literature are listed in the Dosage and Administration section of the product insert.

To report adverse reactions or to obtain a copy of the SDS for this product call 1‑844‑253‑2926. For additional information about adverse drug experience reporting for animal drugs, contact FDA at 1‑888‑FDA‑VETS or online at http://www.fda.gov/reportanimalae.

OVERDOSE

Rapid administration, accidental overdose, or relative overdose due to inadequate dose sparing of ALFAXAN MULTIDOSE IDX in the presence of preanesthetics may cause cardiopulmonary depression. Respiratory arrest (apnea) may be observed. In cases of respiratory depression, stop drug administration, establish a patent airway, and initiate assisted or controlled ventilation with pure oxygen. Cardiovascular depression should be treated with plasma expanders, pressor agents, antiarrhythmic agents or other techniques as appropriate for the observed abnormality.

STORAGE INFORMATION

Store at controlled room temperature 20°C - 25°C (68° to 77°F) with excursions between 15° and 30°C (59° and 86°F). ALFAXAN MULTIDOSE IDX contains preservatives. The product can be used for 56 days after broaching the vial. Any unused ALFAXAN MULTIDOSE IDX remaining after 56 days should be discarded.

HOW SUPPLIED

ALFAXAN MULTIDOSE IDX is supplied in 10 and 20 mL multiple-dose vials containing 10 mg alfaxalone per mL.

Manufactured in Australia by Jurox Pty Limited

Marketed By:

Jurox Inc.

Kansas City, MO 64116

Phone 1-844-253-2926

Distributed by:

Vedco, Inc.

St. Joseph, MO 64507

Alfaxan is a registered trademark of Jurox Pty Limited.

LIST of REFERENCES

1. Scheelings TF, Baker RT, Hammersley G, Hollis K, Elton I, Holz P. A preliminary investigation into the chemical restraint of selected Australian squamate species with Alfaxalone. J Herpetol Med Surg 2011;21(2-3): 63-77.
2. Bertelsen MF, Sauer CD. Alfaxalone anaesthesia in the green iguana (Iguana iguana). Vet Anaesth Analg 2011;38(5):461-6.
3. Knotek Z, Hrdá A, Knotková Z, Trnková S, Babák V. Alfaxalone anaesthesia in the green iguana (Iguana iguana). ACTA VET BRNO 2013;82:109–114.
4. Rowland MN. Fibrosing myopathy of the temporal muscles causing lockjaw in a veiled chameleon (Chamaeleo calyptratus). Vet Rec 2011;169:527b.
5. Doss GA, Fink DM, Sladky KK, Mans C. Comparison of subcutaneous dexmedetomidine-midazolam versus alfaxalone- midazolam sedation in leopard geckos (Eublepharis macularius). Vet Anaesth Analg 2017;44(5):1175-1183.
6. Morici M, DiGiuseppe M, Spadola F, Oliveri M, Knotkova Z, Knotek Z. Intravenous alfaxalone anaesthesia in leopard geckos (Eublepharis macularius). J Exot Pet Med 2018;27(3)11-14.
7. Hoffman EM, Garrett K, Doneley RJT. Pneumocoelom causing cloacal prolapse in a perentie monitor (Varanus giganteus). Australian Veterinary Practitioner 2017;47(4):117-120.
8. Knotek Z. Induction to inhalation anaesthesia in agamid lizards with alfaxalone. Veterinarni Medicina 2017;62(01):41–43.
9. Perrin KL, Bertelsen MF. Intravenous alfaxalone and propofol anesthesia in the bearded dragon (Pogona vitticeps). Herpetol Med Surg 2017;27(3-4):123-126.
10. James LE, Williams CJA, Bertelsen MF, Wang T. Anesthetic induction with alfaxalone in the ball python (Python regius): dose response and effect of injection site. Vet Anaesth Analg 2018;45(3):329-337.
11. Strahl-Heldreth D, Clark-Price SC, Keating SCJ, Graham LF, Chinnadurai SK, Schaeffer. Effect of intracoelomic administration of alfaxalone on the righting reflex and tactile stimulus response of common garter snakes (Thamnophis sirtalis). Am J Vet Res 2019;80(2):144-151.
12. Knotek Z. Alfaxalone as an induction agent for anaesthesia in terrapins and tortoises. Vet Rec 2014;175(13):327.
13. Kischinovsky M, Duse A, Wang T, Bertelsen MF. Intramuscular administration of alfaxalone in red-eared sliders (Trachemys scripta elegans)-effects of dose and body temperature. Vet Anaesth Analg 2013;40(1):13-20.
14. Phillips BE, Posner LP, Lewbart GA, Christiansen EF, Harms CA. Effects of alfaxalone administered intravenously to healthy yearling loggerhead sea turtles (Caretta caretta) at three different doses. J Am Vet Med Assoc 2017;250(8):909-917.
15. Hansen LL, Bertelsen MF. Assessment of the effects of intramuscular administration of alfaxalone with and without medetomidine in Horsfield's tortoises (Agrionemys horsfieldii). Vet Anaesth Analg 2013;40(6):e68-75.
16. Romeijer C, Beaufrère H, Laniesse D, Birch SM, MacKenzie S, Melville L, Moens N. Vomiting and gastrointestinal obstruction in a red-footed tortoise (Chelonoidis carbonaria). J Herpetol Med Surg 2016;26(1–2):32-35.
17. Perpiñán D, Martínez-Silvestre A, Bargalló F, Di Giuseppe M, Orós J, Costa T. Correlation between endoscopic sex determination and gonad histology in pond sliders, Trachemys scripta (Reptilia: Testudines: Emydidae). Acta Herpetologica 2016;11(1): 91-94.
18. Hedley J, Woods S, Eatwell K. The use of negative pressure wound therapy following subcarapacial abscess excision in a tortoise. J Small Anim Pract 2013;54(11):610-613.
19. Adami C, d'Ovidio D, Casoni D. Alfaxalone-butorphanol versus alfaxalone-morphine combination for immersion anaesthesia in oriental fire-bellied toads (Bombina orientalis). Lab Anim 2016;50(3):204-211.
20. Sladakovic I, Johnson RS, Vogelnest L. Evaluation of intramuscular alfaxalone in three Australian frog species (Litoria caerulea, Litoria aurea, Litoria booroolongensis). J Herpetol Med Surg 2014;24(1–2):36-42.
21. McMillan MW, Leece EA. Immersion and branchial/transcutaneous irrigation anaesthesia with alfaxalone in a Mexican axolotl. Vet Anaesth Analg 2011;38(6):619-23.
22. Bauquier SH, Greenwood J, Whittem, T. Evaluation of the sedative and anaesthetic effects of five different concentrations of alfaxalone in goldfish, Carassius auratus. Aquaculture 2013;396-399:119–123.
23. O'Hagan BJ, Raidal SR. Surgical removal of retrobulbar hemangioma in a goldfish (Carassius auratus). Vet Clin North Am Exot Anim Pract 2006;9(3):729-33.
24. Minter LJ, Bailey KM, Harms CA, Lewbart GA, Posner LP. The efficacy of alfaxalone for immersion anesthesia in koi carp (Cyprinus carpio). Vet Anaesth Analg 2014;41(4):398-405.
25. Bugman AM, Langer PT, Hadzima E, Rivas AE, Mitchell MA. Evaluation of the anesthetic efficacy of alfaxalone in oscar fish (Astronotus ocellatus). Am J Vet Res 2016; 77(3):239-244.
26. Farry T, Lau C, Keates H, McEwen M, Woldeyohannes S, Perkins N, Goodwin W. Comparison of two formulations of alfaxalone in laboratory zebrafish (Danio rerio) for use in immersion anaesthesia. Oral abstract. 25th International Veterinary Emergency and Critical Care Society (IVECCS) Symposium, September 7th, 2019, Washington, D.C., USA. Session 171.
27. Balko JA, Lindemann DA, Allender MC, Chinnadurai SK. Evaluation of the anesthetic and cardiorespiratory effects of intramuscular alfaxalone administration and isoflurane in budgerigars (Melopsittacus undulatus) and comparison with manual restraint. J Am Vet Med Assoc 2019;254(12):1427-1435.
28. Escalante GC, Balko JA, Chinnadurai, SK. Comparison of the sedative effects of alfaxalone and butorphanol-midazolam administered intramuscularly in budgerigars (Melopsittacus undulatus). J Av Med Surg 2018;32(4):279-285.
29. Perrin KL, Nielsen JB, Thomsen AF, Bertelsen MF. Alfaxalone anesthesia in the Bengalese finch (Lonchura domestica). J Zoo Wildl Med 2017;48(4):1146-1153.
30. Villaverde-Morcillo S, Benito J, García-Sánchez R, Martín-Jurado O, Gómez de Segura IA. Comparison of isoflurane and alfaxalone (Alfaxan) for the induction of anesthesia in flamingos (Phoenicopterus roseus) undergoing orthopedic surgery. J Zoo Wildl Med 2014;45(2):361-366.
31. Baldrey V. Assessment of alfaxalone as an anaesthetic induction agent in mute swans (Cygnus olor). Submitted in part fulfilment of the requirements for the Royal College of Veterinary Surgeons’ Diploma in Zoological Medicine 2014:1-68.
32. Gaudio E, Voltan L, De Benedictis GM. Alfaxalone anaesthesia in Lemur catta following dexmedetomidine-butorphanol- midazolam sedation. Vet Anaesth Analg 2018;45(3):351-356.
33. Passarelli L, Rosa MG, Gamberini M, Bakola S, Burman KJ, Fattori P, Galletti C. Cortical connections of area V6Av in the macaque: a visual-input node to the eye/hand coordination system. J Neurosci 2011;31(5):1790-1801.
34. Bakker J, Uilenreef JJ, Pelt ER, Brok HP, Remarque EJ, Langermans JA. Comparison of three different sedative-anaesthetic protocols (ketamine, ketamine-medetomidine and alphaxalone) in common marmosets (Callithrix jacchus). BMC Vet Res 2013;9:1-13.
35. Ansel TV, Nour AK, Benavente-Perez A. The effect of anesthesia on blood pressure measured noninvasively by using the tail- cuff method in marmosets (Callithrix jacchus). J Am Assoc Lab Anim Sci 2016;55(5):594-600.
36. Curths C, Wichmann J, Dunker S, Windt H, Hoymann HG, Lauenstein HD, Hohlfeld J, Becker T, Kaup FJ, Braun A, Knauf S. Airway hyper-responsiveness in lipopolysaccharide-challenged common marmosets (Callithrix jacchus). Clin Sci 2014 126(2):155-62.
37. Sadoun A, Strelnikov K, Bonté E, Fonta C, Girard P. Cognitive impairment in a young marmoset reveals lateral ventriculomegaly and a mild hippocampal atrophy: a case report. Sci Rep 2015;5(16046):1-11.
38. Thomas AA, Leach MC, Flecknell PA. An alternative method of endotracheal intubation of common marmosets (Callithrix jacchus). Lab Anim 2012;46(1):71-76.
39. Tremoleda JL, Kerton A, Gsell W. Anaesthesia and physiological monitoring during in vivo imaging of laboratory rodents: considerations on experimental outcomes and animal welfare. EJNMMI Res 2012;2(44):1-23.
40. Siriarchavatana P, Ayers JD, Kendall LV. Anesthetic activity of alfaxalone compared with ketamine in mice. J Am Assoc Lab Anim Sci 2016;55(4):426-30.
41. Higuchi S, Yamada R, Hashimoto A, Miyoshi K, Yamashita K, Ohsugi T. Evaluation of a combination of alfaxalone with medetomidine and butorphanol for inducing surgical anesthesia in laboratory mice. Jpn J Vet Res 2016;64(2):131-139.
42. Lau C, Ranasinghe MG, Shiels I, Keates H, Pasloske K, Bellingham MC. Plasma pharmacokinetics of alfaxalone after a single intraperitoneal or intravenous injection of Alfaxan® in rats. J Vet Pharmacol Ther 2013;36(5):516-20.
43. Reynolds PS, Song SK, Tamariz FJ, Barbee RW. Hypertension and vulnerability to hemorrhagic shock in a rat model. Shock 2015;43(2):148-156.
44. Arenillas M, Gomez de Segura IA. Anaesthetic effects of alfaxalone administered intraperitoneally alone or combined with dexmedetomidine and fentanyl in the rat. Lab Anim 2018;52(6):588-598.
45. White KL, Paine S, Harris J. A clinical evaluation of the pharmacokinetics and pharmacodynamics of intravenous alfaxalone in cyclodextrin in male and female rats following a loading dose and constant rate infusion. Vet Anaesth Analg 2017;44(4):865- 875.
46. d'Ovidio D, Marino F, Noviello E, Lanaro E, Monticelli P, Adami C. Sedative effects of intramuscular alfaxalone in pet guinea pigs (Cavia porcellus). Vet Anaesth Analg 2018;45(2):183-189.
47. Doerning CM, Bradley MP, Lester PA, Nowland MH. Effects of subcutaneous alfaxalone alone and in combination with dexmedetomidine and buprenorphine in guinea pigs (Cavia porcellus). Vet Anaesth Analg 2018;45(5):658-666.
48. Bercier M, Langlois I, Dunn M, Hélie P, Burns P, Gara-Boivin C. Cytological analysis of bronchoalveolar lavage fluid acquired by bronchoscopy in healthy ferrets: A pilot study. Can J Vet Res 2016;80(1):74-80.
49. Thas I. Acquired salivary mucoceles in two domestic ferrets (Mustela putorius furo). Vet Rec Case Rep 2014; 2:1-8.
50. Giral M, García-Olmo DC, Gómez-Juárez M, Gómez de Segura IA. Anaesthetic effects in the ferret of alfaxalone alone and in combination with medetomidine or tramadol: a pilot study. Lab Anim 2014;48(4):313-320.
51. Vogelnest L. Marsupialia (Marsupials). Fowler's Zoo and Wild Animal Medicine. 2014; Volume 8, Chapter 33, p.260.
52. McInnes LM, Gillett A, Ryan UM, Austen J, Campbell RS, Hanger J, Reid SA. Trypanosoma irwini n. sp (Sarcomastigophora: Trypanosomatidae) from the koala (Phascolarctos cinereus). Parasitology 2009;136(8):875-885.
53. McInnes LM, Hanger J, Simmons G, Reid SA, Ryan UM. Novel trypanosome Trypanosoma gilletti sp. (Euglenozoa: Trypanosomatidae) and the extension of the host range of Trypanosoma copemani to include the koala (Phascolarctos cinereus). Parasitology 2011;138(1):59-70.
54. McInnes LM, Gillett A, Hanger J, Reid SA, Ryan UM. The potential impact of native Australian trypanosome infections on the health of koalas (Phascolarctos cinereus). Parasitology 2011;138(7):873-883.
55. Markey B, Wan C, Hanger J, Phillips C, Timms P. Use of quantitative real-time PCR to monitor the shedding and treatment of chlamydiae in the koala (Phascolarctos cinereus). Vet Microbiol 2007;120(3-4):334-342.
56. Waugh C, Khan SA, Carver S, Hanger J, Loader J, Polkinghorne A, Beagley K, Timms P. A prototype recombinant-protein based Chlamydia pecorum vaccine results in reduced chlamydial burden and less clinical disease in free-ranging koalas (Phascolarctos cinereus). PLoS One 2016;11(1):1-9.
57. Liddle V, Naranjo C, Bernays M. Anterior chamber collapse syndrome in a koala. Aust Vet J 2014;92(5):179-182.
58. Bouts T, Karunaratna D, Berry K, Dodds J, Gasthuys F, Routh A, Taylor P. Evaluation of medetomidine-alfaxalone and medetomidine-ketamine in semi-free ranging Bennett's wallabies (Macropus rufogriseus). J Zoo Wildl Med 2011;42(4):617- 622.
59. del Álamo AM, Mandsager RE, Riebold TW, Payton ME. Evaluation of intravenous administration of alfaxalone, propofol, and ketamine-diazepam for anesthesia in alpacas. Vet Anaesth Analg 2015;42(1):72-82.

PRINCIPAL DISPLAY PANEL - 10 mL Vial

CIV

Alfaxan® Multidose

IDX

(alfaxalone) 10 mg/mL

For use as an injectable sedative and anesthetic in multiple non food-producing minor species.

CAUTION: Federal law restricts this drug to use by or on the order of a licensed veterinarian.

10 mL

NDC 49480-003-01

Before using this product, read package insert for complete product information.

Distributed by Vedco, Inc.

Marketed by Jurox Inc. Phone 1-844-253-2926

Legally Marketed - MIF 900-031. Extra-label use is prohibited.

Store at controlled room temperature 20º to 25ºC (68º to 77º F) with excursions between 15° and 30°C (59° and 86°F).

Use within 56 days of first puncture.

PRINCIPAL DISPLAY PANEL - 10 mL Carton

CIV

Alfaxan® Multidose

IDX

(alfaxalone) 10 mg/mL

For use as an injectable sedative and anesthetic in multiple non food-producing minor species.

CAUTION: Federal law restricts this drug to use by or on the order of a licensed veterinarian.

10 mL

This product is INDEXED - MIF 900-031

Principal Display Panel - 20 mL Vial

CIV

Alfaxan® Multidose

IDX

(alfaxalone) 10 mg/mL

For use as an injectable sedative and anesthetic in multiple non food-producing minor species.

CAUTION: Federal law restricts this drug to use by or on the order of a licensed veterinarian.

20 mL

NDC 49480-003-02

Before using this product, read package insert for complete product information.

Distributed by Vedco, Inc.

Marketed by Jurox Inc. Phone 1-844-253-2926

Legally Marketed - MIF 900-031. Extra-label use is prohibited.

Store at controlled room temperature 20º to 25ºC (68º to 77º F) with excursions between 15° and 30°C (59° and 86°F).

Use within 56 days of first puncture.

Principal Display Panel - 20 mL Carton

CIV

Alfaxan® Multidose

IDX

(alfaxalone) 10 mg/mL

For use as an injectable sedative and anesthetic in multiple non food-producing minor species.

CAUTION: Federal law restricts this drug to use by or on the order of a licensed veterinarian.

20 mL

This product is INDEXED - MIF 900-031